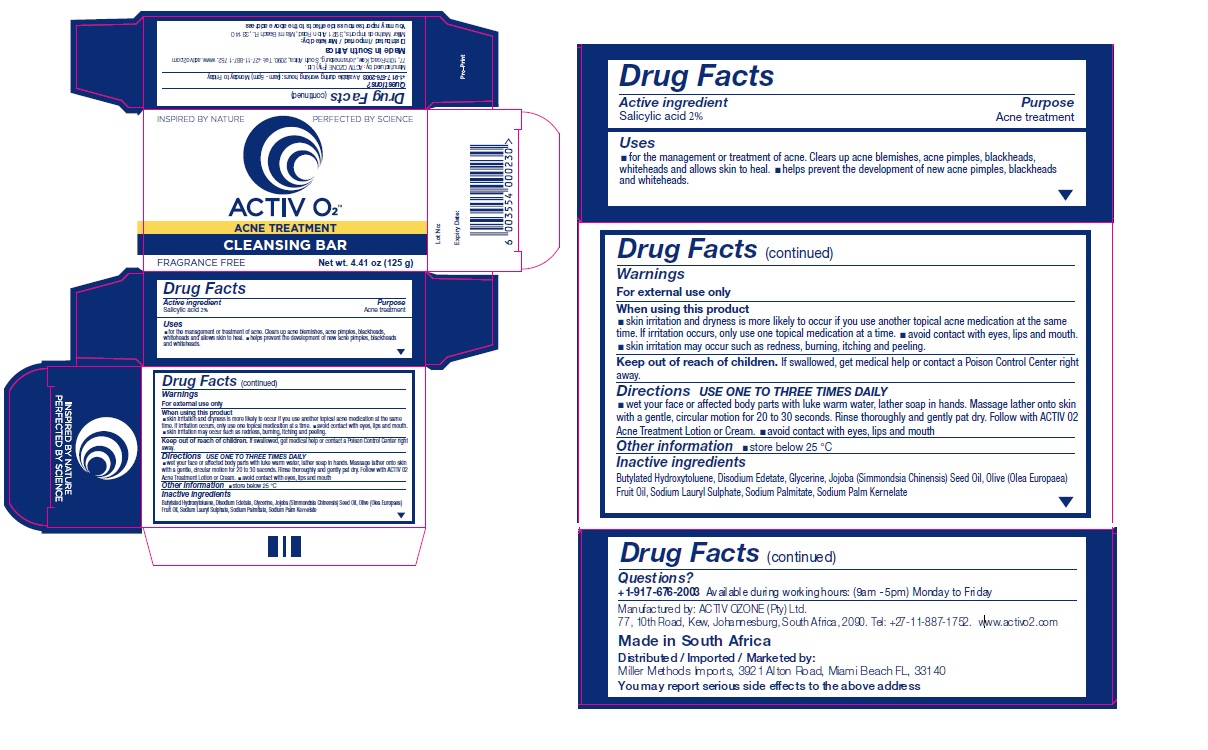 DRUG LABEL: ACTIV O2 ACNE TREATMENT CLEANSING BAR
NDC: 71577-111 | Form: SOAP
Manufacturer: Activ Ozone (pty) Ltd
Category: otc | Type: HUMAN OTC DRUG LABEL
Date: 20170918

ACTIVE INGREDIENTS: SALICYLIC ACID 2 g/100 g
INACTIVE INGREDIENTS: BUTYLATED HYDROXYTOLUENE; EDETATE DISODIUM; GLYCERIN; JOJOBA OIL; OLIVE OIL; SODIUM LAURYL SULFATE; SODIUM PALMITATE; SODIUM PALM KERNELATE

ACTIV O2 ACNE TREATMENT CLEANSING BAR

Active ingredient

Salicylic acid 2%

Purpose

Acne treatment

Uses

• for the management or treatment of acne. Clears up acne blemishes, acne pimples, blackheads, whiteheads, and allows skin to heal. • helps prevent the development of new acne pimples, blackheads and whiteheads.

Warnings

For external use only
When using this product
• skin irritation and dryness is more likely to occur if you use another topical acne medication at the same time. If irritation occurs, only use one topical acne medication at a time. • avoid contact with the eyes, lips and mouth. • skin irritation may occur such as redness, burning, itching and peeling.

Keep out of reach of children. If swallowed, get medical help or contact a Poison Control Center right away.

Directions

USE ONE TO THREE TIMES DAILY

• wet your face or affected body parts with luke warm water, lather soap in hands. Massage lather onto skin with a gentle, circular motion for 20 to 30 seconds. Rinse thoroughly and gently pat dry. Follow with ACTIV O2 Acne Treatment Lotion or Cream. • avoid contact with eyes, lips and mouth

Inactive ingredients

Butylated Hydroxytoluene, Disodium Edetate, Glycerin, Jojoba (Simmondsia Chinensis) Seed Oil, Olive (Olea Europaea) Fruit Oil, Sodium Lauryl Sulphate, Sodium Palmitate, Sodium Palm Kernelate

Other information

• store below 25 °C

Questions?

+1-917-676-2004 Available during working hours: (9am – 5pm) Monday to Friday

Manufactured by: ACTIV OZONE (Pty) Ltd.
77, 10th Road, Kew, Johannesburg, South Arica, 2090. Tel: +27-11-887-1752. www.activo2.com

Made in South Africa

Distributed / Imported / Marketed by:
Miller Methods Imports,3921 Alton Road, Miami Beach FL, 33140
You may report serious side effects to the above address
INSPIRED BY NATURE
PERFECTED BY SCIENCE
FRAGRANCE FREE